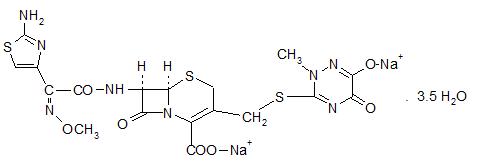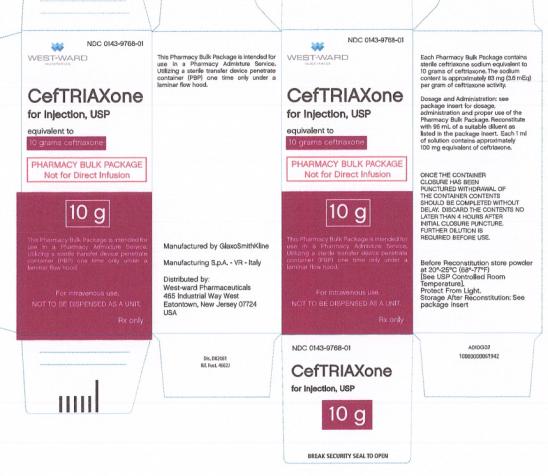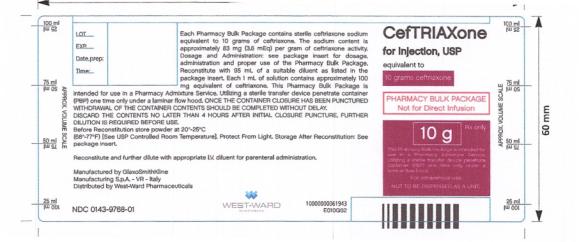 DRUG LABEL: Ceftriaxone
NDC: 0143-9768 | Form: INJECTION, POWDER, FOR SOLUTION
Manufacturer: Hikma Pharmaceuticals USA Inc.
Category: prescription | Type: HUMAN PRESCRIPTION DRUG LABEL
Date: 20191230

ACTIVE INGREDIENTS: CEFTRIAXONE SODIUM 10 g/100 mL

Ceftriaxone for Injection

CEFTRIAXONE FOR INJECTION, USP

PHARMACY BULK PACKAGE
NOT FOR DIRECT INFUSION

Rx only

Issued May 2009

To reduce the development of drug-resistant bacteria and maintain the effectiveness of Ceftriaxone for Injection and other antibacterial drugs, Ceftriaxone should be used only to treat or prevent infections that are proven or strongly suspected to be caused by bacteria.

DESCRIPTION

Ceftriaxone for injection, USP is a sterile, semisynthetic, broad-spectrum cephalosporin antibiotic for intravenous or intramuscular administration. Ceftriaxone sodium is (6R,7R)-7-[2-(2-Amino-4-thiazolyl)glyoxylamido]-8-oxo-3-[[(1,2,5,6-tetrahydro-2-methyl-5,6-dioxo-as-triazin-3-yl)thio]methyl]-5-thia-1-azabicyclo[4.2.0]oct-2-ene-2-carboxylic acid, 7^2-(Z)-(O-methyloxime), disodium salt, sesquaterhydrate.

The chemical formula of ceftriaxone sodium is C18H16N8Na2O7S3•3.5H2O. It has a calculated molecular weight of 661.60 and the following structural formula:

Ceftriaxone for Injection, USP is a white to yellowish-orange crystalline powder which is readily soluble in water, sparingly soluble in methanol and very slightly soluble in ethanol. The pH of a 1% aqueous solution is approximately 6.7. The color of ceftriaxone for injection, USP solutions ranges from light yellow to amber, depending on the length of storage, concentration and diluent used.

Each Pharmacy Bulk Package is supplied as a dry powder in vials containing sterile ceftriaxone sodium, USP equivalent to 10 grams of ceftriaxone and is intended for intravenous infusion only. Ceftriaxone sodium contains approximately 83 mg (3.6 mEq) of sodium per gram of ceftriaxone activity.

A Pharmacy Bulk Package is a container of a sterile preparation for parenteral use that contains many single doses. The contents are intended for use in a pharmacy admixture program and are restricted to the preparation of admixtures for intravenous infusion. (see DOSAGE AND ADMINISTRATION, and DIRECTIONS FOR PROPER USE OF PHARMACY BULK PACKAGE)

CLINICAL PHARMACOLOGY

Average plasma concentrations of ceftriaxone following a single 30-minute intravenous (IV) infusion of a 0.5, 1 or 2 g dose and intramuscular (IM) administration of a single 0.5 (250 mg/mL or 350 mg/mL concentrations) or 1g dose in healthy subjects are presented in Table 1.

TABLE 1. Ceftriaxone Plasma Concentrations After Single Dose Administration
Dose/Route | Average Plasma Concentrations (mcg/mL)
 | 0.5 hr | 1 hr | 2 hr | 4 hr | 6 hr | 8 hr | 12 hr | 16 hr | 24 hr
0.5 g IV* | 82 | 59 | 48 | 37 | 29 | 23 | 15 | 10 | 5
0.5 g IM 250 mg/mL | 22 | 33 | 38 | 35 | 30 | 26 | 16 | ND | 5
0.5 g IM 350 mg/mL | 20 | 32 | 38 | 34 | 31 | 24 | 16 | ND | 5
1 g IV* | 151 | 111 | 88 | 67 | 53 | 43 | 28 | 18 | 9
1 g IM | 40 | 68 | 76 | 68 | 56 | 44 | 29 | ND | ND
2 g IV* | 257 | 192 | 154 | 117 | 89 | 74 | 46 | 31 | 15
* IV doses were infused at a constant rate over 30 minutes.
ND = Not determined.

Ceftriaxone was completely absorbed following IM administration with mean maximum plasma concentrations occurring between 2 and 3 hours post-dose. Multiple IV or IM doses ranging from 0.5 to 2 g at 12- to 24-hour intervals resulted in 15% to 36% accumulation of ceftriaxone above single dose values.

Ceftriaxone concentrations in urine are shown in Table 2.

TABLE 2. Urinary Concentrations of Ceftriaxone After Single Dose Administration
Dose/Route | Average Urinary Concentrations (mcg/mL)
 | 0-2 hr | 2-4 hr | 4-8 hr | 8-12 hr | 12-24 hr | 24-48 hr
0.5 g IV | 526 | 366 | 142 | 87 | 70 | 15
0.5 g IM | 115 | 425 | 308 | 127 | 96 | 28
1 g IV | 995 | 855 | 293 | 147 | 132 | 32
1 g IM | 504 | 628 | 418 | 237 | ND | ND
2 g IV | 2692 | 1976 | 757 | 274 | 198 | 40
ND = Not determined.

Thirty-three percent to 67% of a ceftriaxone dose was excreted in the urine as unchanged drug and the remainder was secreted in the bile and ultimately found in the feces as microbiologically inactive compounds. After a 1 g IV dose, average concentrations of ceftriaxone, determined from 1 to 3 hours after dosing, were 581 mcg/mL in the gallbladder bile, 788 mcg/mL in the common duct bile, 898 mcg/mL in the cystic duct bile, 78.2 mcg/g in the gallbladder wall and 62.1 mcg/mL in the concurrent plasma.

Over a 0.15 to 3 g dose range in healthy adult subjects, the values of elimination half-life ranged from 5.8 to 8.7 hours; apparent volume of distribution from 5.78 to 13.5 L; plasma clearance from 0.58 to 1.45 L/hour; and renal clearance from 0.32 to 0.73 L/hour. Ceftriaxone is reversibly bound to human plasma proteins, and the binding decreased from a value of 95% bound at plasma concentrations of < 25 mcg/mL to a value of 85% bound at 300 mcg/mL. Ceftriaxone crosses the blood placenta barrier.

The average values of maximum plasma concentration, elimination half-life, plasma clearance and volume of distribution after a 50 mg/kg IV dose and after a 75 mg/kg IV dose in pediatric patients suffering from bacterial meningitis are shown in Table 3. Ceftriaxone penetrated the inflamed meninges of infants and pediatric patients; CSF concentrations after a 50 mg/kg IV dose and after a 75 mg/kg IV dose are also shown in Table 3.

TABLE 3. Average Pharmacokinetic Parameters of Ceftriaxone in Pediatric Patients With Meningitis
 | 50 mg/kg IV | 75 mg/kg IV
Maximum Plasma Concentrations (mcg/mL) | 216 | 275
Elimination Half-life (hr) | 4.6 | 4.3
Plasma Clearance (mL/hr/kg) | 49 | 60
Volume of Distribution (mL/kg) | 338 | 373
CSF Concentration - inflamed meninges (mcg/mL) | 5.6 | 6.4
Range (mcg/mL) | 1.3-18.5 | 1.3-44
Time after dose (hr) | 3.7 (± 1.6) | 3.3 (± 1.4)

Compared to that in healthy adult subjects, the pharmacokinetics of ceftriaxone were only minimally altered in elderly subjects and in patients with renal impairment or hepatic dysfunction (Table 4); therefore, dosage adjustments are not necessary for these patients with ceftriaxone dosages up to 2 g per day. Ceftriaxone was not removed to any significant extent from the plasma by hemodialysis; in six of 26 dialysis patients, the elimination rate of ceftriaxone was markedly reduced.

TABLE 4. Average Pharmacokinetic Parameters of Ceftriaxone in Humans
Subject Group | Elimination Half-Life (hr) | Plasma Clearance (L/hr) | Volume of Distribution (L)
Healthy Subjects | 5.8-8.7 | 0.58-1.45 | 5.8-13.5
Elderly Subjects (mean age, 70.5 yr) | 8.9 | 0.83 | 10.7
Patients With Renal Impairment
Hemodialysis Patients (0-5 mL/min)* | 14.7 | 0.65 | 13.7
Severe (5-15 mL/min) | 15.7 | 0.56 | 12.5
Moderate (16-30 mL/min) | 11.4 | 0.72 | 11.8
Mild (31-60 mL/min) | 12.4 | 0.70 | 13.3
Patients With Liver Disease | 8.8 | 1.1 | 13.6

*Creatinine clearance.

The elimination of ceftriaxone is not altered when Ceftriaxone for Injection is co-administered with probenecid.

Pharmacokinetics in the Middle Ear Fluid: In one study, total ceftriaxone concentrations (bound and unbound) were measured in middle ear fluid obtained during the insertion of tympanostomy tubes in 42 pediatric patients with otitis media. Sampling times were from 1 to 50 hours after a single intramuscular injection of 50 mg/kg of ceftriaxone. Mean (± SD) ceftriaxone levels in the middle ear reached a peak of 35 (± 12) mcg/mL at 24 hours, and remained at 19 (± 7) mcg/mL at 48 hours. Based on middle ear fluid ceftriaxone concentrations in the 23 to 25 hour and the 46 to 50 hour sampling time intervals, a half-life of 25 hours was calculated. Ceftriaxone is highly bound to plasma proteins. The extent of binding to proteins in the middle ear fluid is unknown.

Interaction with Calcium: Two in vitro studies, one using adult plasma and the other neonatal plasma from umbilical cord blood have been carried out to assess interaction of ceftriaxone and calcium. Ceftriaxone concentrations up to 1 mM (in excess of concentrations achieved in vivo following administration of 2 grams ceftriaxone infused over 30 minutes) were used in combination with calcium concentrations up to 12 mM (48 mg/dL). Recovery of ceftriaxone from plasma was reduced with calcium concentrations of 6 mM (24 mg/dL) or higher in adult plasma or 4 mM (16 mg/dL) or higher in neonatal plasma. This may be reflective of ceftriaxone-calcium precipitation.

Microbiology: The bactericidal activity of ceftriaxone results from inhibition of cell wall synthesis. Ceftriaxone has a high degree of stability in the presence of beta-lactamases, both penicillinases and cephalosporinases, of gram-negative and gram-positive bacteria.

In an in vitro study antagonistic effects have been observed with the combination of chloramphenicol and ceftriaxone.

Ceftriaxone has been shown to be active against most strains of the following microorganisms, both in vitro and in clinical infections described in the INDICATIONS AND USAGE section.

Aerobic gram-negative microorganisms:
Acinetobacter calcoaceticus
Enterobacter aerogenes
Enterobacter cloacae
Escherichia coli
Haemophilus influenzae (including ampicillin-resistant and beta-lactamase producing strains)
Haemophilus parainfluenzae
Klebsiella oxytoca
Klebsiella pneumoniae
Moraxella catarrhalis (including beta-lactamase producing strains)
Morganella morganii
Neisseria gonorrhoeae (including penicillinase- and nonpenicillinase-producing strains)
Neisseria meningitidis
Proteus mirabilis
Proteus vulgaris
Serratia marcescens

Ceftriaxone is also active against many strains of Pseudomonas aeruginosa.

NOTE: Many strains of the above organisms that are resistant to multiple antibiotics, e.g., penicillins, cephalosporins, and aminoglycosides, are susceptible to ceftriaxone.

Aerobic gram-positive microorganisms:
Staphylococcus aureus (including penicillinase-producing strains)
Staphylococcus epidermidis
Streptococcus pneumoniae
Streptococcus pyogenes
Viridans group streptococci

NOTE: Methicillin-resistant staphylococci are resistant to cephalosporins, including ceftriaxone. Most strains of Group D streptococci and enterococci, e.g., Enterococcus (Streptococcus) faecalis, are resistant.

Anaerobic microorganisms:
Bacteroides fragilis
Clostridium species
Peptostreptococcus species

NOTE: Most strains of Clostridium difficile are resistant.

The following in vitro data are available, but their clinical significance is unknown. Ceftriaxone exhibits in vitro minimal inhibitory concentrations (MICs) of ≤ 8 mcg/mL or less against most strains of the following microorganisms, however, the safety and effectiveness of ceftriaxone in treating clinical infections due to these microorganisms have not been established in adequate and well-controlled clinical trials.

Aerobic gram-negative microorganisms:
Citrobacter diversus
Citrobacter freundii
Providencia species (including Providencia rettgeri)
Salmonella species (including Salmonella typhi)
Shigella species

Aerobic gram-positive microorganisms:
Streptococcus agalactiae

Anaerobic microorganisms:
Prevotella (Bacteroides) bivius
Porphyromonas (Bacteroides) melaninogenicus

Susceptibility Tests:

Dilution Techniques:

Quantitative methods are used to determine antimicrobial minimal inhibitory concentrations (MICs). These MICs provide estimates of the susceptibility of bacteria to antimicrobial compounds. The MICs should be determined using a standardized procedure.^1 Standardized procedures are based on a dilution method (broth or agar) or equivalent with standardized inoculum concentrations and standardized concentrations of ceftriaxone powder. The MIC values should be interpreted according to the following criteria^2 for aerobic organisms other than Haemophilus spp, Neisseria gonorrhoeae, and Streptococcus spp, including Streptococcus pneumoniae:

MIC (mcg/mL) | Interpretation
≤ 8 | (S) Susceptible
16-32 | (I) Intermediate
≥ 64 | (R) Resistant

The following interpretive criteria^2 should be used when testing Haemophilus species using Haemophilus Test Media (HTM).

MIC (mcg/mL) | Interpretation
≤ 2 | (S) Susceptible

The absence of resistant strains precludes defining any categories other than "Susceptible". Strains yielding results suggestive of a "Nonsusceptible" category should be submitted to a reference laboratory for further testing.

The following interpretive criteria^2 should be used when testing Neisseria gonorrhoeae when using GC agar base and 1% defined growth supplement.

MIC (mcg/mL) | Interpretation
≤ 0.25 | (S) Susceptible

The absence of resistant strains precludes defining any categories other than "Susceptible". Strains yielding results suggestive of a "Nonsusceptible" category should be submitted to a reference laboratory for further testing.

The following interpretive criteria^2 should be used when testing Streptococcus spp including Streptococcus pneumoniae using cation-adjusted Mueller-Hinton broth with 2 to 5% lysed horse blood.

MIC (mcg/mL) | Interpretation
≤ 0.5 | (S) Susceptible
1 | (I) Intermediate
≥ 2 | (R) Resistant

A report of "Susceptible" indicates that the pathogen is likely to be inhibited if the antimicrobial compound in the blood reaches the concentrations usually achievable. A report of "Intermediate" indicates that the results should be considered equivocal, and if the microorganism is not fully susceptible to alternative, clinically feasible drugs, the test should be repeated. This category implies possible clinical applicability in body sites where the drug is physiologically concentrated or in situations where high dosage of the drug can be used. This category also provides a buffer zone which prevents small uncontrolled technical factors from causing major discrepancies in interpretation. A report of "Resistant" indicates that the pathogen is not likely to be inhibited if the antimicrobial compound in the blood reaches the concentrations usually achievable; other therapy should be selected.

Standardized susceptibility test procedures require the use of laboratory control microorganisms to control the technical aspects of the laboratory procedures. Standardized ceftriaxone powder should provide the following MIC values:^2

Microorganism | ATCC® # | MIC (mcg/mL)
Escherichia coli | 25922 | 0.03-0.12
Staphylococcus aureus | 29213 | 1-8*
Pseudomonas aeruginosa | 27853 | 8-32
Haemophilus influenzae | 49247 | 0.06-0.25
Neisseria gonorrhoeae | 49226 | 0.004-0.015
Streptococcus pneumoniae | 49619 | 0.03-0.12
* A bimodal distribution of MICs results at the extremes of the acceptable range should be suspect and control validity should be verified with data from other control strains.
ATCC® is a registered trademark of the American Type Culture Collection.

Diffusion Techniques:

Quantitative methods that require measurement of zone diameters also provide reproducible estimates of the susceptibility of bacteria to antimicrobial compounds. One such standardized procedure^3 requires the use of standardized inoculum concentrations. This procedure uses paper discs impregnated with 30 mcg of ceftriaxone to test the susceptibility of microorganisms to ceftriaxone.

Reports from the laboratory providing results of the standard single-disc susceptibility test with a 30 mcg ceftriaxone disc should be interpreted according to the following criteria for aerobic organisms other than Haemophilus spp, Neisseria gonorrhoeae, and Streptococcus spp:

Zone Diameter (mm) | Interpretation
≥ 21 | (S) Susceptible
14-20 | (I) Intermediate
≤ 13 | (R) Resistant

The following interpretive criteria^3 should be used when testing Haemophilus species when using Haemophilus Test Media (HTM).

Zone Diameter (mm) | Interpretation
≥ 26 | (S) Susceptible

The absence of resistant strains precludes defining any categories other than “Susceptible”. Strains yielding results suggestive of a “Nonsusceptible” category should be submitted to a reference laboratory for further testing.

The following interpretive criteria^3 should be used when testing Neisseria gonorrhoeae when using GC agar base and 1% defined growth supplement.

Zone Diameter (mm) | Interpretation
≥ 35 | (S) Susceptible

The absence of resistant strains precludes defining any categories other than “Susceptible”. Strains yielding results suggestive of a “Nonsusceptible” category should be submitted to a reference laboratory for further testing.

The following interpretive criteria^3 should be used when testing Streptococcus spp other than Streptococcus pneumoniae when using Mueller-Hinton agar supplemented with 5% sheep blood incubated in 5% CO2.

Zone Diameter (mm) | Interpretation
≥ 27 | (S) Susceptible
25-26 | (I) Intermediate
≤ 24 | (R) Resistant

Interpretation should be as stated above for results using dilution techniques. Interpretation involves correlation of the diameter obtained in the disc test with the MIC for ceftriaxone.

Disc diffusion interpretive criteria for ceftriaxone discs against Streptococcus pneumoniae are not available, however, isolates of pneumococci with oxacillin zone diameters of > 20mm are susceptible (MIC ≤ 0.06 mcg/mL) to penicillin and can be considered susceptible to ceftriaxone. Streptococcus pneumoniae isolates should not be reported as penicillin (ceftriaxone) resistant or intermediate based solely on an oxacillin zone diameter of ≤ 19mm. The ceftriaxone MIC should be determined for those isolates with oxacillin zone diameters ≤ 19mm.

As with standardized dilution techniques, diffusion methods require the use of laboratory control microorganisms that are used to control the technical aspects of the laboratory procedures. For the diffusion technique, the 30 mcg ceftriaxone disc should provide the following zone diameters in these laboratory test quality control strains:^3

Microorganism | ATCC® # | Zone Diameter Ranges (mm)
Escherichia coli | 25922 | 29-35
Staphylococcus aureus | 25923 | 22-28
Pseudomonas aeruginosa | 27853 | 17-23
Haemophilus influenzae | 49247 | 31-39
Neisseria gonorrhoeae | 49226 | 39-51
Streptococcus pneumoniae | 49619 | 30-35

Anaerobic Techniques:

For anaerobic bacteria, the susceptibility to ceftriaxone as MICs can be determined by standardized test methods.^4 The MIC values obtained should be interpreted according to the following criteria:

MIC (mcg/mL) | Interpretation
≤ 16 | (S) Susceptible
32 | (I) Intermediate
≥ 64 | (R) Resistant

As with other susceptibility techniques, the use of laboratory control microorganisms is required to control the technical aspects of the laboratory standardized procedures. Standardized ceftriaxone powder should provide the following MIC values for the indicated standardized anaerobic dilution^4 testing method:

Method | Microorganism | ATCC® # | MIC (mcg/mL)
Agar | Bacteroides fragilis | 25285 | 32 - 128
 | Bacteroides thetaiotaomicron | 29741 | 64 - 256
Broth | Bacteroides thetaiotaomicron | 29741 | 32 - 128

INDICATIONS AND USAGE

Before instituting treatment with Ceftriaxone for Injection, appropriate specimens should be obtained for isolation of the causative organism and for determination of its susceptibility to the drug. Therapy may be instituted prior to obtaining results of susceptibility testing.

To reduce the development of drug-resistant bacteria and maintain the effectiveness of Ceftriaxone for Injection and other antibacterial drugs, Ceftriaxone for Injection should be used only to treat or prevent infections that are proven or strongly suspected to be caused by susceptible bacteria. When culture and susceptibility information are available, they should be considered in selecting or modifying antibacterial therapy. In the absence of such data, local epidemiology and susceptibility patterns may contribute to the empiric selection of therapy.

Ceftriaxone for Injection is indicated for the treatment of the following infections when caused by susceptible organisms:

LOWER RESPIRATORY TRACT INFECTIONS caused by Streptococcus pneumoniae, Staphylococcus aureus, Haemophilus influenzae, Haemophilus parainfluenzae, Klebsiella pneumoniae, Escherichia coli, Enterobacter aerogenes, Proteus mirabilis or Serratia marcescens.

ACUTE BACTERIAL OTITIS MEDIA caused by Streptococcus pneumoniae, Haemophilus influenzae (including beta-lactamase producing strains) or Moraxella catarrhalis (including beta-lactamase producing strains).

NOTE: In one study lower clinical cure rates were observed with a single dose of Ceftriaxone for Injection compared to 10 days of oral therapy. In a second study comparable cure rates were observed between single dose Ceftriaxone for Injection and the comparator. The potentially lower clinical cure rate of Ceftriaxone for Injection should be balanced against the potential advantages of parenteral therapy (see CLINICAL STUDIES).

SKIN AND SKIN STRUCTURE INFECTIONS caused by Staphylococcus aureus, Staphylococcus epidermidis, Streptococcus pyogenes, Viridans group streptococci, Escherichia coli, Enterobacter cloacae, Klebsiella oxytoca, Klebsiella pneumoniae, Proteus mirabilis, Morganella morganii,* Pseudomonas aeruginosa, Serratia marcescens, Acinetobacter calcoaceticus, Bacteroides fragilis* or Peptostreptococcus species.

URINARY TRACT INFECTIONS (complicated and uncomplicated) caused by Escherichia coli, Proteus mirabilis, Proteus vulgaris, Morganella morganii or Klebsiella pneumoniae.

UNCOMPLICATED GONORRHEA (cervical/urethral and rectal) caused by Neisseria gonorrhoeae, including both penicillinase- and nonpenicillinase-producing strains, and pharyngeal gonorrhea caused by nonpenicillinase-producing strains of Neisseria gonorrhoeae.

PELVIC INFLAMMATORY DISEASE caused by Neisseria gonorrhoeae. Ceftriaxone for Injection, like other cephalosporins, has no activity against Chlamydia trachomatis. Therefore, when cephalosporins are used in the treatment of patients with pelvic inflammatory disease and Chlamydia trachomatis is one of the suspected pathogens, appropriate antichlamydial coverage should be added.

BACTERIAL SEPTICEMIA caused by Staphylococcus aureus, Streptococcus pneumoniae, Escherichia coli, Haemophilus influenzae or Klebsiella pneumoniae.

BONE AND JOINT INFECTIONS caused by Staphylococcus aureus, Streptococcus pneumoniae, Escherichia coli, Proteus mirabilis, Klebsiella pneumoniae or Enterobacter species.

INTRA-ABDOMINAL INFECTIONS caused by Escherichia coli, Klebsiella pneumoniae, Bacteroides fragilis, Clostridium species (Note: most strains of Clostridium difficile are resistant) or Peptostreptococcus species.

MENINGITIS caused by Haemophilus influenzae, Neisseria meningitidis or Streptococcus pneumoniae. Ceftriaxone for Injection has also been used successfully in a limited number of cases of meningitis and shunt infection caused by Staphylococcus epidermidis* and Escherichia coli*.

*Efficacy for this organism in this organ system was studied in fewer than ten infections.

SURGICAL PROPHYLAXIS: The preoperative administration of a single 1 g dose of Ceftriaxone for Injection may reduce the incidence of postoperative infections in patients undergoing surgical procedures classified as contaminated or potentially contaminated (e.g., vaginal or abdominal hysterectomy or cholecystectomy for chronic calculous cholecystitis in high-risk patients, such as those over 70 years of age, with acute cholecystitis not requiring therapeutic antimicrobials, obstructive jaundice or common duct bile stones) and in surgical patients for whom infection at the operative site would present serious risk (e.g., during coronary artery bypass surgery). Although Ceftriaxone for Injection has been shown to have been as effective as cefazolin in the prevention of infection following coronary artery bypass surgery, no placebo-controlled trials have been conducted to evaluate any cephalosporin antibiotic in the prevention of infection following coronary artery bypass surgery.

When administered prior to surgical procedures for which it is indicated, a single 1 g dose of Ceftriaxone for Injection provides protection from most infections due to susceptible organisms throughout the course of the procedure.

CONTRAINDICATIONS

Ceftriaxone for Injection is contraindicated in patients with known allergy to the cephalosporin class of antibiotics.

Neonates (≤ 28 days)

Hyperbilirubinemic neonates, especially prematures, should not be treated with Ceftriaxone for Injection. In vitro studies have shown that ceftriaxone can displace bilirubin from its binding to serum albumin and bilirubin encephalopathy can possibly develop in these patients.

Ceftriaxone for Injection is contraindicated in neonates if they require (or are expected to require) treatment with calcium-containing IV solutions, including continuous calcium-containing infusions such as parenteral nutrition because of the risk of precipitation of ceftriaxone-calcium (see CLINICAL PHARMACOLOGY, WARNINGS and DOSAGE AND ADMINISTRATION).

A small number of cases of fatal outcomes in which a crystalline material was observed in the lungs and kidneys at autopsy have been reported in neonates receiving Ceftriaxone for Injection and calcium-containing fluids. In some of these cases, the same intravenous infusion line was used for both Ceftriaxone for Injection and calcium-containing fluids and in some a precipitate was observed in the intravenous infusion line. At least one fatality has been reported in a neonate in whom Ceftriaxone for Injection and calcium-containing fluids were administered at different time points via different intravenous lines; no crystalline material was observed at autopsy in this neonate. There have been no similar reports in patients other than neonates.

WARNINGS

Hypersensitivity

BEFORE THERAPY WITH CEFTRIAXONE FOR INJECTION IS INSTITUTED, CAREFUL INQUIRY SHOULD BE MADE TO DETERMINE WHETHER THE PATIENT HAS HAD PREVIOUS HYPERSENSITIVITY REACTIONS TO CEPHALOSPORINS, PENICILLINS OR OTHER DRUGS. THIS PRODUCT SHOULD BE GIVEN CAUTIOUSLY TO PENICILLIN-SENSITIVE PATIENTS. ANTIBIOTICS SHOULD BE ADMINISTERED WITH CAUTION TO ANY PATIENT WHO HAS DEMONSTRATED SOME FORM OF ALLERGY, PARTICULARLY TO DRUGS. SERIOUS ACUTE HYPERSENSITIVITY REACTIONS MAY REQUIRE THE USE OF SUBCUTANEOUS EPINEPHRINE AND OTHER EMERGENCY MEASURES.

Interaction with Calcium-Containing Products

Do not use diluents containing calcium, such as Ringer’s solution or Hartmann’s solution, to reconstitute Ceftriaxone for Injection vials or to further dilute a reconstituted vial for IV administration because a precipitate can form. Precipitation of ceftriaxone-calcium can also occur when Ceftriaxone for Injection is mixed with calcium-containing solutions in the same IV administration line. Ceftriaxone for Injection must not be administered simultaneously with calcium-containing IV solutions, including continuous calcium-containing infusions such as parenteral nutrition via a Y-site. However, in patients other than neonates, Ceftriaxone for Injection and calcium-containing solutions may be administered sequentially of one another if the infusion lines are thoroughly flushed between infuions with a compatible fluid. In vitro studies using adult and neonatal plasma from umbilical cord blood demonstrated that neonates have an increased risk of precipitation of ceftriaxone-calcium (see CLINICAL PHARMACOLOGY, CONTRAINDICATIONS and DOSAGE AND ADMINISTRATION).

Clostridium difficile

Clostridium difficile associated diarrhea (CDAD) has been reported with use of nearly all antibacterial agents, including Ceftriaxone for Injection, and may range in severity from mild diarrhea to fatal colitis. Treatment with antibacterial agents alters the normal flora of the colon leading to overgrowth of C. difficile.

C difficile produces toxins A and B which contribute to the development of CDAD. Hypertoxin producing strains of C. difficile cause increased morbidity and mortality, as these infections can be refractory to antimicrobial therapy and may require colectomy. CDAD must be considered in all patients who present with diarrhea following antibiotic use. Careful medical history is necessary since CDAD has been reported to occur over two months after the administration of antibacterial agents.

If CDAD is suspected or confirmed, ongoing antibiotic use not directed against C. difficile may need to be discontinued. Appropriate fluid and electrolyte management, protein supplementation, antiobiotic treatment of C. difficile, and surgical evaluation should be instituted as clinically indicated.

PRECAUTIONS

General

Prescribing Ceftriaxone for Injection in the absence of a proven or strongly suspected bacterial infection or a prophylactic indication is unlikely to provide benefit to the patient and increases the risk of the development of drug-resistant bacteria.

Although transient elevations of BUN and serum creatinine have been observed, at the recommended dosages, the nephrotoxic potential of Ceftriaxone for Injection is similar to that of other cephalosporins.

Ceftriaxone is excreted via both biliary and renal excretion (see CLINICAL PHARMACOLOGY). Therefore, patients with renal failure normally require no adjustment in dosage when usual doses of Ceftriaxone for Injection are administered.

Dosage adjustments should not be necessary in patients with hepatic dysfunction; however, in patients with both hepatic dysfunction and significant renal disease, caution should be exercised and the Ceftriaxone for Injection dosage should not exceed 2 g daily.

Alterations in prothrombin times have occurred rarely in patients treated with Ceftriaxone for Injection. Patients with impaired vitamin K synthesis or low vitamin K stores (e.g., chronic hepatic disease and malnutrition) may require monitoring of prothrombin time during Ceftriaxone for Injection treatment. Vitamin K administration (10 mg weekly) may be necessary if the prothrombin time is prolonged before or during therapy.

Prolonged use of Ceftriaxone for Injection may result in overgrowth of nonsusceptible organisms. Careful observation of the patient is essential. If superinfection occurs during therapy, appropriate measures should be taken.

Ceftriaxone for Injection should be prescribed with caution in individuals with a history of gastrointestinal disease, especially colitis.

There have been reports of sonographic abnormalities in the gallbladder of patients treated with Ceftriaxone for Injection; some of these patients also had symptoms of gallbladder disease. These abnormalities appear on sonography as an echo without acoustical shadowing suggesting sludge or as an echo with acoustical shadowing which may be misinterpreted as gallstones. The chemical nature of the sonographically detected material has been determined to be predominantly a ceftriaxone-calcium salt. The condition appears to be transient and reversible upon discontinuation of Ceftriaxone for Injection and institution of conservative management. Therefore, Ceftriaxone for Injection should be discontinued in patients who develop signs and symptoms suggestive of gallbladder disease and/or the sonographic findings described above.

Cases of pancreatitis, possibly secondary to biliary obstruction, have been reported rarely in patients treated with Ceftriaxone for Injection. Most patients presented with risk factors for biliary stasis and biliary sludge (preceding major therapy, severe illness, total parenteral nutrition). A cofactor role of Ceftriaxone for Injection-related biliary precipitation cannot be ruled out.

As with other cephalosporins, anaphylactic shock cannot be ruled out even if a thorough patient history is taken.

Information for Patients:

Patients should be counseled that antibacterial drugs including Ceftriaxone for Injection should only be used to treat bacterial infections. They do not treat viral infections (e.g., common cold). When Ceftriaxone for Injection is prescribed to treat a bacterial infection, patients should be told that although it is common to feel better early in the course of therapy, the medication should be taken exactly as directed. Skipping doses or not completing the full course of therapy may (1) decrease the effectiveness of the immediate treatment and (2) increase the likelihood that bacteria will develop resistance and will not be treatable by Ceftriaxone for Injection or other antibacterial drugs in the future.

Diarrhea is a common problem caused by antibiotics which usually ends when the antibiotic is discontinued. Sometimes after starting treatment with antibiotics, patients can develop watery and bloody stools (with or without stomach cramps and fever) even as late as two or more months after having taken the last dose of the antibiotic. If this occurs, patients should contact their physician as soon as possible.

Carcinogenesis, Mutagenesis, Impairment of Fertility:

Carcinogenesis:

Considering the maximum duration of treatment and the class of the compound, carcinogenicity studies with ceftriaxone in animals have not been performed. The maximum duration of animal toxicity studies was 6 months.

Mutagenesis:

Genetic toxicology tests included the Ames test, a micronucleus test and a test for chromosomal aberrations in human lymphocytes cultured in vitro with ceftriaxone. Ceftriaxone showed no potential for mutagenic activity in these studies.

Impairment of Fertility:

Ceftriaxone produced no impairment of fertility when given intravenously to rats at daily doses up to 586 mg/kg/day, approximately 20 times the recommended clinical dose of 2 g/day.

Pregnancy:

Teratogenic Effects:

Pregnancy Category B. Reproductive studies have been performed in mice and rats at doses up to 20 times the usual human dose and have no evidence of embryotoxicity, fetotoxicity or teratogenicity. In primates, no embryotoxicity or teratogenicity was demonstrated at a dose approximately 3 times the human dose.

There are, however, no adequate and well-controlled studies in pregnant women. Because animal reproductive studies are not always predictive of human response, this drug should be used during pregnancy only if clearly needed.

Nonteratogenic Effects:

In rats, in the Segment I (fertility and general reproduction) and Segment III (perinatal and postnatal) studies with intravenously administered ceftriaxone, no adverse effects were noted on various reproductive parameters during gestation and lactation, including postnatal growth, functional behavior and reproductive ability of the offspring, at doses of 586 mg/kg/day or less.

Nursing Mothers:

Low concentrations of ceftriaxone are excreted in human milk. Caution should be exercised when Ceftriaxone for Injection is administered to a nursing woman.

Pediatric Use:

Safety and effectiveness of Ceftriaxone for Injection in neonates, infants and pediatric patients have been established for the dosages described in the DOSAGE AND ADMINISTRATION section. In vitro studies have shown that ceftriaxone, like some other cephalosporins, can displace bilirubin from serum albumin. Ceftriaxone for Injection should not be administered to hyperbilirubinemic neonates, especially prematures (see CONTRAINDICATIONS).

Geriatric Use:

Of the total number of subjects in clinical studies of Ceftriaxone for Injection, 32% were 60 and over. No overall differences in safety or effectiveness were observed between these subjects and younger subjects, and other reported clinical experience has not identified differences in responses between the elderly and younger patients, but greater sensitivity of some older individuals cannot be ruled out.

The pharmacokinetics of ceftriaxone were only minimally altered in geriatric patients compared to healthy adult subjects and dosage adjustments are not necessary for geriatric patients with ceftriaxone dosages up to 2 grams per day (see CLINICAL PHARMACOLOGY).

ADVERSE REACTIONS

Ceftriaxone for Injection is generally well tolerated. In clinical trials, the following adverse reactions, which were considered to be related to Ceftriaxone for Injection therapy or of uncertain etiology, were observed:

LOCAL REACTIONS — pain, induration and tenderness was 1% overall. Phlebitis was reported in <1% after IV administration. The incidence of warmth, tightness or induration was 17% (3/17) after IM administration of 350 mg/mL and 5% (1/20) after IM administration of 250 mg/mL.

HYPERSENSITIVITY — rash (1.7%). Less frequently reported (<1%) were pruritus, fever or chills.

HEMATOLOGIC — eosinophilia (6%), thrombocytosis (5.1%) and leukopenia (2.1%). Less frequently reported (<1%) were anemia, hemolytic anemia, neutropenia, lymphopenia, thrombocytopenia and prolongation of the prothrombin time.

GASTROINTESTINAL — diarrhea (2.7%). Less frequently reported (<1%) were nausea or vomiting, and dysgeusia. The onset of pseudomembranous colitis symptoms may occur during or after antibacterial treatment (see WARNINGS).

HEPATIC — elevations of SGOT (3.1%) or SGPT (3.3%). Less frequently reported (<1%) were elevations of alkaline phosphatase and bilirubin.

RENAL — elevations of the BUN (1.2%). Less frequently reported (< 1%) were elevations of creatinine and the presence of casts in the urine.

CENTRAL NERVOUS SYSTEM — headache or dizziness were reported occasionally (<1 %).

GENITOURINARY — moniliasis or vaginitis were reported occasionally (<1%).

MISCELLANEOUS — diaphoresis and flushing were reported occasionally (<1%).

Other rarely observed adverse reactions (< 0.1%) include abdominal pain, agranulocytosis, allergic pneumonitis, anaphylaxis, basophilia, biliary lithiasis, bronchospasm, colitis, dyspepsia, epistaxis, flatulence, gallbladder sludge, glycosuria, hematuria, jaundice, leukocytosis, lymphocytosis, monocytosis, nephrolithiasis, palpitations, a decrease in the prothrombin time, renal precipitations, seizures, and serum sickness.

Postmarketing Experience:

In addition to the adverse reactions reported during clinical trials, the following adverse experiences have been reported during clinical practice in patients treated with Ceftriaxone for Injection. Data are generally insufficient to allow an estimate of incidence or to establish causation.

A small number of cases of fatal outcomes in which a crystalline material was observed in the lungs and kidneys at autopsy have been reported in neonates receiving Ceftriaxone for Injection and calcium-containing fluids. In some of these cases, the same intravenous infusion line was used for both Ceftriaxone for Injection and calcium-containing fluids and in some a precipitate was observed in the intravenous infusion line. At least one fatality has been reported in a neonate in whom Ceftriaxone for Injection and calcium-containing fluids were administered at different time points via different intravenous lines; no crystalline material was observed at autopsy in this neonate. There have been no similar reports in patients other than neonates.

GASTROINTESTINAL — stomatitis and glossitis.

GENITOURINARY — oliguria.

DERMATOLOGIC — exanthema, allergic dermatitis, urticaria, edema. As with many medications, isolated cases of severe cutaneous adverse reactions (erythema multiforme, Stevens-Johnson syndrome or Lyell’s syndrome/toxic epidermal necrolysis) have been reported.

Cephalosporin Class Adverse Reactions

In addition to the adverse reactions listed above which have been observed in patients treated with ceftriaxone, the following adverse reactions and altered laboratory test results have been reported for cephalosporin class antibiotics:

Adverse Reactions: Allergic reactions, drug fever, serum sickness-like reaction, renal dysfunction, toxic nephropathy, reversible hyperactivity, hypertonia, hepatic dysfunction including cholestasis, aplastic anemia, hemorrhage, and superinfection.

Altered Laboratory Tests: Positive direct Coombs’ test, false-positive test for urinary glucose, and elevated LDH.

Several cephalosporins have been implicated in triggering seizures, particularly in patients with renal impairment when the dosage was not reduced (see DOSAGE AND ADMINISTRATION). If seizures associated with drug therapy occur, the drug should be discontinued. Anticonvulsant therapy can be given if clinically indicated.

OVERDOSAGE

In the case of overdosage, drug concentration would not be reduced by hemodialysis or peritoneal dialysis. There is no specific antidote. Treatment of overdosage should be symptomatic.

DOSAGE AND ADMINISTRATION

Ceftriaxone for Injection may be administered intravenously or intramuscularly. However, the intent of this Pharmacy Bulk Package is for the preparation of solutions for intravenous infusion only. Ceftriaxone should be administered intravenously by infusion over a period of 30 minutes.

Do not use diluents containing calcium, such as Ringer’s solution or Hartmann’s solution, to reconstitute Ceftriaxone for Injection vials or to further dilute a reconstituted vial for IV administration because a precipitate can form. Precipitation of ceftriaxone-calcium can also occur when Ceftriaxone for Injection is mixed with calcium-containing solutions in the same IV administration line. Ceftriaxone for Injection must not be administered simultaneously with calcium-containing IV solution, including continuous calcium-containing infusions such as parenteral nutrition via a Y-site. However, in patients in other than neonates, Ceftriaxone for Injection and calcium-containing solutions may be administered sequentially of one another if the infusion lines are thoroughly flushed between infusions with a compatible fluid (see WARNINGS).

There have been no reports of an interaction between ceftriaxone and oral calcium-containing products or interaction between intramuscular ceftriaxone and calcium-containing products (IV or oral).

NEONATES: Hyperbilirubinemic neonates, especially prematures, should not be treated with Ceftriaxone for Injection (see CONTRAINDICATIONS).

Ceftriaxone is contraindicated in neonates if they require (or are expected to require) treatment with calcium-containing IV solutions, including continuous calcium-containing infusions such as parenteral nutrition because of the risk of precipitation of ceftriaxone-calcium (see CONTRAINDICATIONS).

PEDIATRIC PATIENTS: For the treatment of skin and skin structure infections, the recommended total daily dose is 50 to 75 mg/kg given once a day (or in equally divided doses twice a day). The total daily dose should not exceed 2 grams.

For the treatment of acute bacterial otitis media, a single intramuscular dose of 50 mg/kg (not to exceed 1 gram) is recommended (see INDICATIONS AND USAGE).

For the treatment of serious miscellaneous infections other than meningitis, the recommended total daily dose is 50 to 75 mg/kg, given in divided doses every 12 hours. The total daily dose should not exceed 2 grams.

In the treatment of meningitis, it is recommended that the initial therapeutic dose be 100 mg/kg (not to exceed 4 grams). Thereafter, a total daily dose of 100 mg/kg/day (not to exceed 4 grams daily) is recommended. The daily dose may be administered once a day (or in equally divided doses every 12 hours). The usual duration of therapy is 7 to 14 days.

ADULTS: The usual adult daily dose is 1 to 2 grams given once a day (or in equally divided doses twice a day) depending on the type and severity of infection. The total daily dose should not exceed 4 grams.

If Chlamydia trachomatis is a suspected pathogen, appropriate antichlamydial coverage should be added, because ceftriaxone sodium has no activity against this organism.

For the treatment of uncomplicated gonococcal infections, a single intramuscular dose of 250 mg is recommended.

For preoperative use (surgical prophylaxis), a single dose of 1 gram administered intravenously 1/2 to 2 hours before surgery is recommended.

Generally, Ceftriaxone for Injection therapy should be continued for at least 2 days after the signs and symptoms of infection have disappeared. The usual duration of therapy is 4 to 14 days; in complicated infections, longer therapy may be required.

When treating infections caused by Streptococcus pyogenes, therapy should be continued for at least 10 days.

No dosage adjustment is necessary for patients with impairment of renal or hepatic function.

DIRECTIONS FOR PROPER USE OF PHARMACY BULK PACKAGE:

The 10 gram vial should be reconstituted with 95 mL of an appropriate IV diluent in a suitable work area such as a laminar flow hood. The resulting solution will contain approximately 100 mg/mL of ceftriaxone. This closure may be penetrated only one time after reconstitution, using a suitable sterile transfer device or dispensing set which allows measured dispensing of the contents.

The withdrawal of container contents should be accomplished without delay. However, should this not be possible, a maximum time of 4 HOURS from initial closure entry is permitted to complete fluid transfer operations. Unused portions of solution held longer than the recommended time periods should be discarded.

Reconstituted Bulk Solutions Should Not Be Used For Direct Infusion.

Transfer individual dose to appropriate intravenous solutions as soon as possible following reconstitution of the bulk package. The stability of the solution that has been transferred into a container varies according to diluent, concentration and temperature (see COMPATIBILITY AND STABILITY). Concentrations between 10 mg/mL and 40 mg/mL are recommended; however, lower concentrations may be used if desired.

COMPATABILITY AND STABILITY: Ceftriaxone has been shown to be compatible with Flagyl® IV* (metronidazole hydrochloride). The concentration should not exceed 5 to 7.5 mg/mL metronidazole hydrochloride with ceftriaxone 10 mg/mL as an admixture. The admixture is stable for 24 hours at room temperature only in 0.9% sodium chloride injection or 5% dextrose in water (D5W). No compatability studies have been conducted with the Flagyl® IV RTU® (metronidazole) formulation or using other diluents. Metronidazole at concentrations greater than 8 mg/mL will precipitate. Do not refrigerate the admixture as precipitation will occur.

*Registered trademark of G.D. Searle & Co.

Vancomycin, amsacrine, aminoglycosides, and fluconazole are physically incompatible with ceftriaxone in admixtures. When any of these drugs are to be administered concomitantly with ceftriaxone by intermittent intravenous infusion, it is recommended that they be given sequentially, with thorough flushing of the intravenous lines (with one of the compatible fluids) between the administrations.

Do not use diluents containing calcium, such as Ringer’s solution or Hartmann’s solution, to reconstitute Ceftriaxone for Injection vials or to further dilute a reconstituted vial for IV administration. Particulate formation can result.

Ceftriaxone for Injection solutions should not be physically mixed with or piggybacked into solutions containing other antimicrobial drugs or into diluent solutions other than those listed above, due to possible incompatibility (see WARNINGS).

Ceftriaxone for Injection sterile powder should be stored at 20 - 25°C (68 - 77°F) [See USP Controlled Room Temperature] and protected from light. After reconstitution, protection from normal light is not necessary. The color of solutions ranges from light yellow to amber, depending on the length of storage, concentration and diluent used.

Ceftriaxone for Injection intravenous solutions, at concentrations of 10, 20, and 40 mg/mL, remain stable (loss of potency less than 10%) for the following time periods stored in glass or PVC containers:

 | Storage
Diluent | Room Temp. (25°C) | Refrigerated (4°C)
Sterile Water | 2 days | 10 days
0.9% Sodium Chloride Solution | 2 days | 10 days
5% Dextrose Solution | 2 days | 10 days
10% Dextrose Solution | 2 days | 10 days
5% Dextrose + 0.9% Sodium Chloride Solution [Data available for 10 to 40 mg/mL concentrations in this diluent in PVC containers only.] | 2 days | Incompatible
5% Dextrose + 0.45% Sodium Chloride Solution | 2 days | Incompatible

The following intravenous Ceftriaxone for Injection solutions are stable at room temperature (25 °C) for 24 hours, at concentrations between 10 mg/mL and 40 mg/mL: Sodium Lactate (PVC container), 10% Invert Sugar (glass container), 5% Sodium Bicarbonate (glass container), Freamine III (glass container), Normosol-M in 5% Dextrose (glass and PVC containers), Ionosol-B in 5% Dextrose (glass container), 5% Mannitol (glass container), 10% Mannitol (glass container).

After the indicated stability time periods, unused portions of solutions should be discarded.

NOTE: Parenteral drug products should be inspected visually for particulate matter before administration.

Ceftriaxone for Injection reconstituted with 5% Dextrose or 0.9% Sodium Chloride solution at concentrations between 10 mg/mL and 40 mg/mL, and then stored in frozen state (- 20°C) in PVC or polyolefin containers, remains stable for 26 weeks.

Frozen solutions of Ceftriaxone for Injection should be thawed at room temperature before use. After thawing, unused portions should be discarded. DO NOT REFREEZE.

ANIMAL PHARMACOLOGY

Concretions consisting of the precipitated calcium salt of ceftriaxone have been found in the gallbladder bile of dogs and baboons treated with ceftriaxone.

These appeared as a gritty sediment in dogs that received 100 mg/kg/day for 4 weeks. A similar phenomenon has been observed in baboons but only after a protracted dosing period (6 months) at higher dose levels (335 mg/kg/day or more). The likelihood of this occurrence in humans is considered to be low, since ceftriaxone has a greater plasma half-life in humans, the calcium salt of ceftriaxone is more soluble in human gallbladder bile and the calcium content of human gallbladder bile is relatively low.

HOW SUPPLIED

Ceftriaxone for Injection, USP is available in Pharmacy Bulk Packages containing 10 g equivalent of ceftriaxone. Box of 1 (NDC 0143-9768-01).

NOTE: Ceftriaxone for Injection sterile powder should be stored at 20 - 25°C (68 - 77°F) [See USP Controlled Room Temperature] and protected from light.

CLINICAL STUDIES

Clinical Trials in Pediatric Patients With Acute Bacterial Otitis Media

In two adequate and well-controlled U.S. clinical trials a single IM dose of ceftriaxone was compared with a 10 day course of oral antibiotic in pediatric patients between the ages of 3 months and 6 years. The clinical cure rates and statistical outcome appear in the table below:

Clinical Efficacy in Evaluable Population
Study Day | Ceftriaxone Single Dose | Comparator – 10 Days of Oral Therapy | 95% Confidence Interval | Statistical Outcome
Study 1 – U.S. |  | amoxicillin/clavulanate |  | Ceftriaxone is lower than control at study day 14 and 28.
14 | 74% (220/296) | 82% (247/302) | (-14.4%, -0.5%)
28 | 58% (167/288) | 67% (200/297) | (-17.5%, -1.2%)
Study 2 – U.S.^5 |  | TMP-SMZ |  | Ceftriaxone is equivalent to control at study day 14 and 28.
14 | 54% (113/210) | 60% (124/206) | (-16.4%, 3.6%)
28 | 35% (73/206) | 45% (93/205) | (-19.9%, 0.0%)

An open-label bacteriologic study of ceftriaxone without a comparator enrolled 108 pediatric patients, 79 of whom had positive baseline cultures for one or more of the common pathogens. The results of this study are tabulated as follows:

Week 2 and 4 Bacteriologic Eradication Rates in the Per Protocol Analysis in the Roche Bacteriologic Study by pathogen:

 | Study Day 13-15 |  | Study Day 30+2
Organism | No. Analyzed | No. Erad. (%) | No. Analyzed | No. Erad. (%)
Streptococcus pneumoniae | 38 | 32 (84) | 35 | 25 (71)
Haemophilus influenzae | 33 | 28 (85) | 31 | 22 (71)
Moraxella catarrhalis | 15 | 12 (80) | 15 | 9 (60)

REFERENCES

1. National Committee for Clinical Laboratory Standards, Methods for Dilution Antimicrobial Susceptibility Tests for Bacteria that Grow Aerobically; Approved Standard-Fifth Edition. NCCLS document M7-A5 (ISBN 1-56238-309-9). NCCLS, Wayne, PA 19087-1898, 2000.
2. National Committee for Clinical Laboratory Standards, Supplemental Tables. NCCLS document M100-S10(M7) (ISBN 1-56238-309-9). NCCLS, Wayne, PA 19087-1898, 2000.
3. National Committee for Clinical Laboratory Standards, Performance Standards for Antimicrobial Disk Susceptibility Tests; Approved Standard-Seventh Edition. NCCLS document M2-A7 (ISBN 1-56238-393-0). NCCLS, Wayne, PA 19087-1898, 2000.
4. National Committee for Clinical Laboratory Standards, Methods for Antimicrobial Susceptibility Testing of Anaerobic Bacteria; Approved Standard-Fourth Edition. NCCLS document M11-A4 (ISBN 1-56238-210-1). NCCLS, Wayne, PA 19087 1898, 1997.
5. Barnett ED, Teele DW, Klein JO, et al. Comparison of Ceftriaxone and Trimethoprim-Sulfamethoxazole for Acute Otitis Media. Pediatrics. Vol. 99, No.1, January 1997.

Manufactured by: GlaxoSmithKline Manufacturing S.p.A. - Verona - Italy

Distributed by: West-Ward Injectables - Eatontown - New Jersey - USA

Issued May 2009